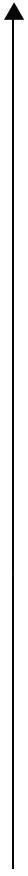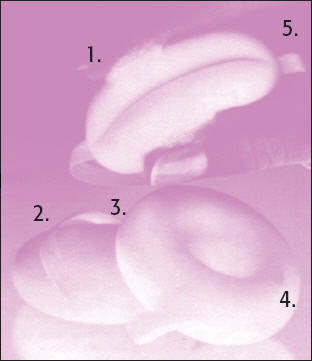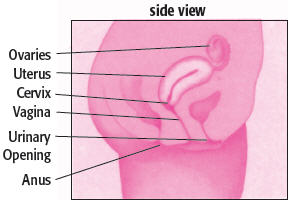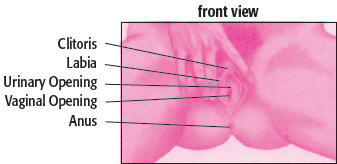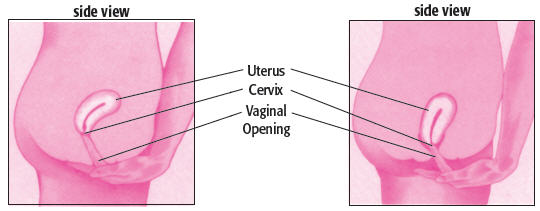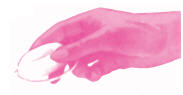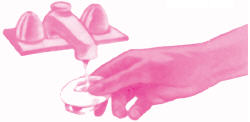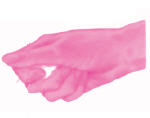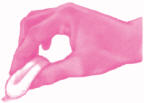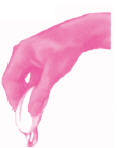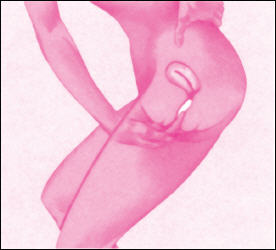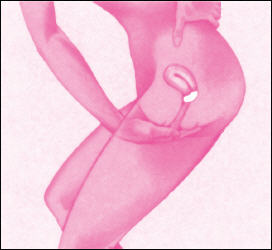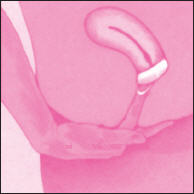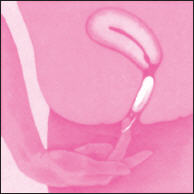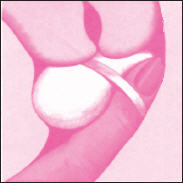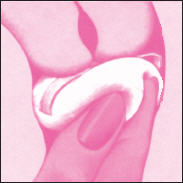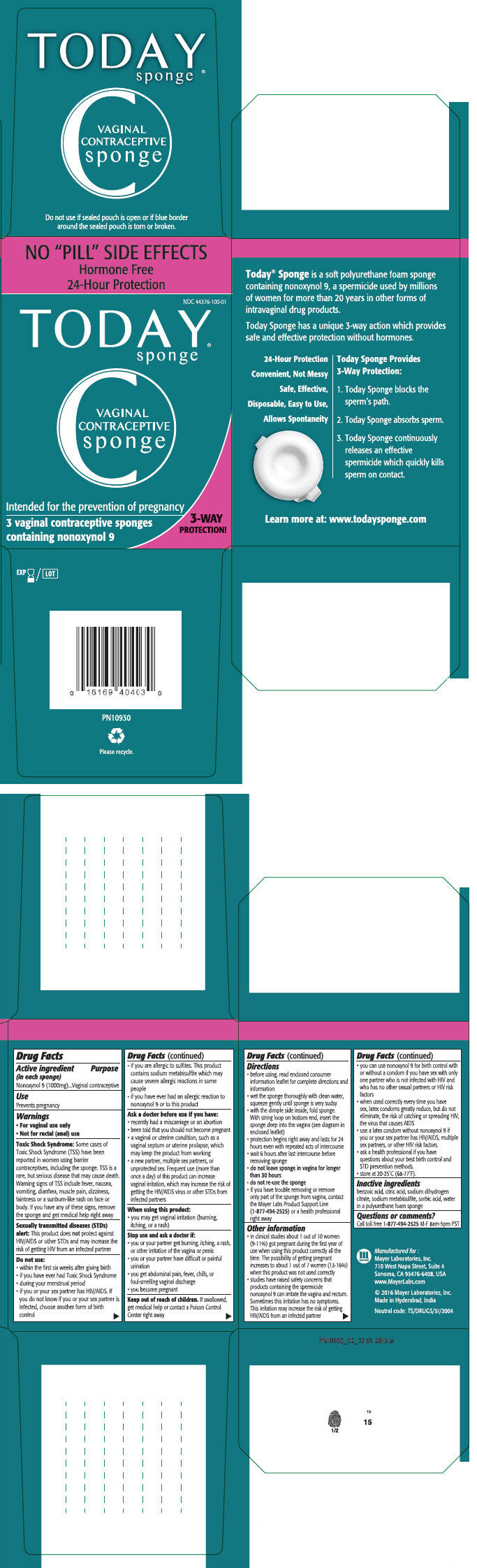 DRUG LABEL: Today Vaginal Contraceptive
NDC: 44376-100 | Form: SPONGE
Manufacturer: Mayer Laboratories, Inc.
Category: otc | Type: HUMAN OTC DRUG LABEL
Date: 20180119

ACTIVE INGREDIENTS: Nonoxynol-9 1000 mg/1 1
INACTIVE INGREDIENTS: benzoic acid; citric acid monohydrate; monosodium citrate; sodium metabisulfite; sorbic acid; water; urethane

TODAY® Vaginal Contraceptive Sponge

Drug Facts

Active ingredient (in each sponge)

Nonoxynol 9 (1000mg)

Purpose

Vaginal contraceptive

Use

Prevents pregnancy

Warnings

- For vaginal use only
- Not for rectal (anal) use

Toxic Shock Syndrome

Some cases of Toxic Shock Syndrome (TSS) have been reported in women using barrier contraceptives, including the sponge. TSS is a rare, but serious disease that may cause death. Warning signs of TSS include fever, nausea, vomiting, diarrhea, muscle pain, dizziness, faintness or a sunburn-like rash on face or body. If you have any of these signs, remove the sponge and get medical help right away

Sexually transmitted diseases (STDs) alert

This product does not protect against HIV/AIDS or other STDs and may increase the risk of getting HIV from an infected partner

Do not use

- within the first six weeks after giving birth
- if you have ever had Toxic Shock Syndrome
- during your menstrual period
- if you or your sex partner has HIV/AIDS. If you do not know if you or your sex partner is infected, choose another form of birth control
- if you are allergic to sulfites. This product contains sodium metabisulfite which may cause severe allergic reactions in some people
- if you have ever had an allergic reaction to nonoxynol 9 or to this product

Ask a doctor before use if you have

- recently had a miscarriage or an abortion
- been told that you should not become pregnant
- a vaginal or uterine condition, such as a vaginal septum or uterine prolapse, which may keep the product from working
- a new partner, multiple sex partners, or unprotected sex. Frequent use (more than once a day) of this product can increase vaginal irritation, which may increase the risk of getting the HIV/AIDS virus or other STDs from infected partners

When using this product

- you may get vaginal irritation (burning, itching, or a rash)

Stop use and ask a doctor if

- you or your partner get burning, itching, a rash, or other irritation of the vagina or penis
- you or your partner have difficult or painful urination
- you get abdominal pain, fever, chills, or foul-smelling vaginal discharge
- you become pregnant

Keep out of reach of children. If swallowed, get medical help or contact a Poison Control Center right away.

Directions

- before using, read enclosed consumer information leaflet for complete directions and information
- wet the sponge thoroughly with clean water, squeeze gently until sponge is very sudsy
- with the dimple side inside, fold sponge. With string loop on bottom end, insert the sponge deep into the vagina (see diagram in enclosed leaflet)
- protection begins right away and lasts for 24 hours even with repeated acts of intercourse
- wait 6 hours after last intercourse before removing sponge
- do not leave sponge in vagina for longer than 30 hours
- do not re-use the sponge
- if you have trouble removing or remove only part of the sponge from vagina, contact the Mayer Labs Product Support Line (1-877-494-2525) or a health professional right away

Other information

- in clinical studies about 1 out of 10 women (9-11%) got pregnant during the first year of use when using this product correctly all the time. The possibility of getting pregnant increases to about 1 out of 7 women (13-16%) when this product was not used correctly
- studies have raised safety concerns that products containing the spermicide nonoxynol 9 can irritate the vagina and rectum. Sometimes this irritation has no symptoms. This irritation may increase the risk of getting HIV/AIDS from an infected partner
- you can use nonoxynol 9 for birth control with or without a condom if you have sex with only one partner who is not infected with HIV and who has no other sexual partners or HIV risk factors
- when used correctly every time you have sex, latex condoms greatly reduce, but do not eliminate, the risk of catching or spreading HIV, the virus that causes AIDS
- use a latex condom without nonoxynol 9 if you or your sex partner has HIV/AIDS, multiple sex partners, or other HIV risk factors
- ask a health professional if you have questions about your best birth control and STD prevention methods
- store at 20-25°C (68-77°F)

Inactive ingredients

benzoic acid, citric acid, sodium dihydrogen citrate, sodium metabisulfite, sorbic acid, water in a polyurethane foam sponge.

Questions or comments?

Call toll free 1-877-494-2525 M-F 8am-5pm PST

PATIENT INFORMATION

Vaginal Contraceptive Sponge

This 24-hour vaginal contraceptive sponge is intended for the prevention of pregnancy.

Consumer Information Leaflet

Your Personal Guide

Please read the Drug Facts label on the carton and this leaflet completely and carefully before using Today® Sponge. If used correctly according to the label and diagram instructions on back of leaflet, Today® Sponge may be a safe, effective and convenient birth control method.

IMPORTANT INFORMATION FOR USERS

If you have no previous experience with vaginal birth control products, you should contact a doctor, health professional or family planning clinic for advice on how to use this product correctly. If you have any questions on the best birth control method for you, contact a doctor, health professional or a family health clinic, especially if:

- You were told that you should not become pregnant
- You have given birth before

No birth control product can prevent pregnancy all the time. See Table of Pregnancy Rates for Birth Control Methods for a comparison of pregnancy rates.

No birth control method is without side effects or is suitable for all women. Consult a health professional for your best method.

For best results, barrier methods, such as the sponge or condom, must be used correctly during every act of intercourse.

Pregnancy Rates for Birth Control Methods

(For One Year of Use)

In clinical studies with Today® Sponge, the pregnancy rates per 100 women during the first year of use were:

- About 1 out of 10 women (9-11%) became pregnant when using this correctly all the time.
- The possibility of getting pregnant increased to about 1 out of 7 women (13-16%) when this product was not used correctly.

The following table gives the approximate number of women out of 100 women who are likely to become pregnant while using a particular contraceptive method for one year.

Pregnancy Rates for Birth Control Methods

Number of Women Out of 100 Women Who Will Become Pregnant in the First Year of Use

Table A
Most Effective (Fewer Pregnancies) Least Effective (More Pregnancies) | Method | Number of women out of 100 who will become pregnant in one year of typical use ["Typical Use" means use that is less than perfect. Sometimes women do not use a method correctly or with every sexual act of intercourse.]
Most Effective (Fewer Pregnancies) Least Effective (More Pregnancies) | - Sterilization (male or female) - Intrauterine Devices (IUDs) | Less than 1
Most Effective (Fewer Pregnancies) Least Effective (More Pregnancies) | - Hormonal Methods: - Implant | Less than 1
Most Effective (Fewer Pregnancies) Least Effective (More Pregnancies) | - Injection | 3
Most Effective (Fewer Pregnancies) Least Effective (More Pregnancies) | - Pill - Patch - Vaginal Ring | 8
Most Effective (Fewer Pregnancies) Least Effective (More Pregnancies) | - Male condoms (used without spermicide) | 15
Most Effective (Fewer Pregnancies) Least Effective (More Pregnancies) | - Lea's Shield (used with spermicide) | 15 [Clinical trial product data submitted to FDA]
Most Effective (Fewer Pregnancies) Least Effective (More Pregnancies) | - Diaphragm (used with spermicide) | 16
Most Effective (Fewer Pregnancies) Least Effective (More Pregnancies) | - Vaginal Sponge (contains spermicide) - Cervical Cap (use with spermicide)
Most Effective (Fewer Pregnancies) Least Effective (More Pregnancies) | ▸ 16 for women who have never had children ▸ 32 for women who have had one or more children | 16-32
Most Effective (Fewer Pregnancies) Least Effective (More Pregnancies) | - Female Condom | 21
Most Effective (Fewer Pregnancies) Least Effective (More Pregnancies) | - Withdrawal - Natural Family Planning (calendar, temperature, cervical mucus) | 25 - 27
Most Effective (Fewer Pregnancies) Least Effective (More Pregnancies) | - Spermicides alone (gel, cream, foam, film, suppository) | 29
Most Effective (Fewer Pregnancies) Least Effective (More Pregnancies) | - No contraception | 85

Data adapted from: Trussell J. Contraceptive Efficacy. In Hatcher RA, Trussell J, Stewart F, et al. Contraceptive Technology: Nineteenth Revised Edition. New York, NY: Ardent Media, 2007.

1. PRODUCT OVERVIEW

A. What is Today Vaginal Contraceptive Sponge and how does it work?

This birth control product is a soft, disposable polyurethane foam sponge containing 1000 mg of nonoxynol 9, which kills sperm on contact. It is inserted into the vagina and while in place provides protection against pregnancy for 24 hours. As long as the sponge is in place in the vagina, there is no need to add additional spermicidal creams or jellies, even if intercourse is repeated.

Used as directed, Today® Sponge prevents pregnancy in three ways: 1) the nonoxynol 9 contained in Today® Sponge kills sperm before they can reach the egg; 2) Today® Sponge blocks the cervix opening to the uterus so the sperm cannot enter; 3) Today® Sponge traps and absorbs the sperm.

1. Nonoxynol 9 contained within the sponge is released gradually over a 24-hour period.
2. Soft polyurethane foam sponge is formulated to feel like normal vaginal tissue.
3. Specially designed ribbon loop is attached to an interior web for maximum strength for removing sponge.
4. Anatomically contoured indentation covers cervix to help position sponge properly.
5. Sponge exterior is carefully shaped for easy insertion.
6. Store Today® Sponge at 20-25°C (68-77°F).

B. How can I improve the effectiveness of the Today Vaginal Contraceptive Sponge?

No birth control method can provide reliable protection if it is not used correctly and consistently.

For greater birth control protection, you may want to use another method of birth control in addition to using the sponge, especially during the first few months while you become familiar with how to use it.

Correct use of a latex condom by your partner together with your correct use of the Today® Sponge may provide additional protection against getting pregnant.

C. How easy is it to use Today Vaginal Contraceptive Sponge?

This product is designed to be convenient and easy to use, and to avoid interruption of lovemaking, because it can be inserted up to 24 hours before starting intercourse. Protection begins right away and lasts for 24 hours even with repeated acts of intercourse. However the sponge should remain in place for at least 6 hours after the last act of intercourse, but should not be left in the vagina longer than 30 hours.

Any woman who can use a tampon should not have difficulty using the sponge. It does not require a special fitting or prescription.

2. WARNINGS

- For vaginal use only
- Not for rectal (anal) use

Toxic Shock Syndrome: Some cases of Toxic Shock Syndrome (TSS) have been reported in women using barrier contraceptives, including the sponge. TSS is a rare, but serious disease that may cause death. Warning signs of TSS include fever, nausea, vomiting, diarrhea, muscle pain, dizziness, faintness or a sunburn-like rash on face or body. If you have any of these signs, remove the sponge and get medical help right away. You can avoid the risk of getting sponge-associated TSS by not using the sponge

Sexually transmitted diseases (STDs) alert: This product does not protect against HIV/AIDS or other STDs and may increase the risk of getting HIV from an infected partner

Do not use

- within the first six weeks after giving birth
- if you have ever had Toxic Shock Syndrome
- during your menstrual period
- if you or your sex partner has HIV/AIDS. If you do not know if you or your sex partner is infected, choose another form of birth control
- if you are allergic to sulfites. This product contains sodium metabisulfite which may cause severe allergic reactions in some people
- if you have ever had an allergic reaction to nonoxynol 9 or to this product

Ask a doctor before use if you have

- recently had a miscarriage or an abortion
- been told that you should not become pregnant
- a vaginal or uterine condition, such as a vaginal septum or uterine prolapse, which may keep the product from working
- signs of pregnancy such as a late menstrual period
- a new partner, multiple sex partners, or unprotected sex. Frequent use (more than once a day) of this product can increase vaginal irritation, which may increase the risk of getting the HIV/AIDS virus or other STDs from infected partners. Ask a doctor or health professional for your best birth control method

When using this product

- you may get vaginal irritation (burning, itching, or a rash)

Stop use and ask a doctor if

- you or your partner get burning, itching, a rash, or other irritation of the vagina or penis
- you or your partner have difficult or painful urination
- you get abdominal pain, fever, chills, or a foul-smelling vaginal discharge
- you become pregnant

Keep out of reach of children. If swallowed, get medical help or contact a Poison Control Center right away. (For most people, ingestion of small quantities of spermicide alone should not be harmful.)

3. DIRECTIONS

Before using, read the back of this leaflet for diagram instructions for inserting and removing sponge.

- Wash hands before use.
- Remove the sponge from the pouch.
- Wet the sponge thoroughly with clean water, squeeze gently several times until sponge is very sudsy.
- With the dimple side of the sponge facing up, fold sponge upward and insert the sponge deep into the vagina as shown in diagram (see section 9). The ribbon loop must be on the bottom for easy removal.
- Protection begins right away and lasts for 24 hours even with repeated acts of intercourse.
- Wait at least 6 hours after the last intercourse before removing sponge.
- Do not leave sponge in vagina for longer than 30 hours. Leaving the sponge in vagina longer than 30 hours may increase the chances for vaginal irritation and serious infections.
- Do not re-use the sponge
- If you have trouble removing the sponge from your vagina or remove only part of the sponge, call the Mayer Labs Product Support Line at 1-877-494-2525 or contact a health professional right away.
- Do not douche while sponge is in your vagina.

Douching is not necessary. If you want to douche wait at least 6 hours after last intercourse and remove the sponge before douching.

4. INACTIVE INGREDIENTS

Benzoic acid, citric acid, sodium dihydrogen citrate, sodium metabisulfite, sorbic acid, water in a polyurethane foam sponge.

5. OTHER INFORMATION

- studies have raised safety concerns that products containing the spermicide nonoxynol 9 can irritate the vagina and rectum. Sometimes this irritation has no symptoms. This irritation may increase the risk of getting HIV/AIDS from an infected partner
- you can use nonoxynol 9 for birth control with or without a condom if you have sex with only one partner who is not infected with HIV and who has no other sexual partners or HIV risk factors
- when used correctly every time you have sex, latex condoms greatly reduce, but do not eliminate, the risk of catching or spreading HIV, the virus that causes AIDS, and other STDs from infected partners
- use a latex condom without nonoxynol 9 if you or your sex partner has HIV/AIDS, multiple sex partners, or other HIV risk factors
- ask a health professional if you have questions about your best birth control and STD prevention methods
- store at 20-25°C (68-77°F)

6. OTHER QUESTIONS YOU MAY HAVE

A. How can I reduce the chances of a serious infection including sexually transmitted diseases (STDs)?

- Read Warnings and Other Information sections before use.
- You may want to see a doctor or health professional for advice on how to reduce the risk of STDs, especially if you have a new sex partner or multiple sex partners.
- Correct use of a latex condom by your partner with every sexual act will help reduce the risk of transmission of the human immunodeficiency virus (HIV) and acquired immunodeficiency syndrome (AIDS) and many sexually transmitted diseases (STDs).
- Do not leave the sponge in vagina longer than 30 hours.
- Make sure that all of sponge is removed from vagina.
- Wash hands before inserting and removing the sponge.

B. Can I use Today® Sponge during my menstrual period?

- Today® Sponge should not be used during the menstrual period. Some cases of Toxic Shock Syndrome have been reported in women using the sponge during their menstrual period.

C. Can I have an allergic reaction or other side effects from the Today® Sponge?

- If you have ever had a severe allergic reaction to sulfites, do not use this product because it contains sodium metabisulfite.
- A small number of men and women may be sensitive to the spermicide, nonoxynol 9, in this product and you should not use this product if irritation occurs and persists. Of the women in clinical trials, between 2-3% discontinued use of the sponge because of itching, irritation, or rash, and 1-3% discontinued because of allergic reactions.

D. What if Today® Sponge develops an odor?

- It is unlikely that you will notice an odor while Today® Sponge is in place. If there is a noticeable odor when you remove the sponge, do not be concerned. Any material placed in the vagina will occasionally produce an odor when exposed to normal vaginal fluids and semen.

E. Can I insert Today® Sponge after intercourse?

- No, the sponge must be inserted before intercourse begins. Once the penis enters the vagina, there is a greater chance of getting pregnant because there may be the leakage of sperm without ejaculation and, with ejaculation, sperm reaches the fallopian tubes even more quickly.

F. How does Today® Sponge stay in place? Can the sponge get lost in my body?

- Today® Sponge is held in place by the muscles of the upper vagina. The cup-like indention in the sponge helps to keep it in place directly over the cervix.
  The opening from the vagina to the uterus is far too small for the sponge to pass through. There is no other normal opening in the vagina that would provide access to any other part of your body.

G. Can Today® Sponge tear while it is in place?

- Today® Sponge should not tear with normal muscular movement within the vagina or even during intercourse. Be careful not to push a fingernail through the sponge when inserting or removing the sponge. There may be minor separation or "splitting" of sponge material at stress points around the ribbon loop or in the center of the indentation. But these minor separations do not affect the contraceptive capabilities of Today® Sponge in any way.

H. What if I have trouble removing Today® Sponge?

- If you have trouble removing the sponge or think that parts of the sponge are still in your vagina, carefully follow the removal instructions on the back of this leaflet. If you still have trouble removing the sponge call the Mayer Labs Product Support Line at 1-877-494-2525 or contact a health professional right away.

I. Can my partner feel Today® Sponge during intercourse?

- Today® Sponge is designed to be soft and comfortable. It feels like normal vaginal tissue. Some men may feel the sponge during intercourse, but this is usually not objectionable.

J. Can I leave Today® Sponge in place when I swim or bathe?

- Yes. Today® Sponge will not be affected in any way.

K. Is Today® Sponge as effective as the pill or IUD?

- No. Today® Sponge is not as effective as the pill or IUD. See Table of Pregnancy Rates for Birth Control Methods.

L. Can I use Today® Sponge more than once?

- No. Use Today® Sponge as directed and dispose of the used sponge in a waste container. Do not flush it down the toilet.

Additional questions or comments?

Call toll free1-877-494-2525 M-F 8am-5pm PST

7. Important Points to Remember

- If you are unsure about how to use Today Vaginal Contraceptive Sponge, contact a doctor, health professional, or family planning clinic for help. | - Today® Sponge contains enough spermicide for repeated acts of intercourse during a 24-hour period.
- To avoid introducing germs into your vagina, always wash your hands before handling Today® Sponge and before inserting your fingers into your vagina. | - It is not necessary to use the sponge for a full 24 hours, as long as it is left in place 6 hours after the last act of intercourse.
- Wetting Today® Sponge with clean water is important. This is what activates the spermicide. You will notice light foam or "suds". Do not try to rinse this out. | - If you have intercourse when sponge has been in place for 24 hours, leave it in place an additional 6 hours after intercourse before removing it. Today® Sponge must not be left in place for more than 30 hours.
- You may insert Today Vaginal Contraceptive Sponge any time up to 24 hours before beginning intercourse. After inserting the sponge, you may have intercourse right away. | - If you have trouble removing the sponge or if you remove only part of the sponge call the Mayer Labs Product Support Line 1-877-494-2525 or contact a health professional right away.

8. Some basic information about your reproductive system

A. To use this method effectively, it is important for you to understand your anatomy.

B. How do I find the vaginal opening?

Today Vaginal Contraceptive Sponge is inserted through the vaginal opening and placed in the deepest part of the vagina, just below the cervix. The cervix is at the bottom end of the uterus, and has a small opening through which sperm must travel to reach and fertilize the egg.

Sit on the edge of a chair with knees apart. Place a good source of light about an arm's length in front of you and use a hand mirror to examine the region between the outer "lips," or labia. The vaginal opening is between the labia, just below the small urinary opening and one or two inches below the clitoris.

C. How do I find the cervix?

D. Bearing Down

It is easier to find the cervix if you squat. Insert your finger gently into the vagina, reaching up on an angle toward the back until you find the firm, round surface of the cervix. It feels something like the tip of your nose. In some cases, it may be difficult to locate, so you may have to explore a bit before you find it.

You can bring your cervix down closer to the vaginal opening, and thus make it easier to locate, by bearing down. Take a deep breath and bear down as if you were having a bowel movement. You should now be able to locate your cervix just above the vaginal opening. This technique is also very useful for removing the sponge.

9. How to insert Today Vaginal Contraceptive Sponge

A. Insertion Procedure

The sponge may be inserted any time up to 24 hours before intercourse.

1. Remove the sponge from the airtight plastic pouch and hold it in one hand with the "dimple" side up. The loop should dangle under the sponge.
2. Wet the sponge thoroughly with clean tap water. The water activates the spermicide.
3. Squeeze the sponge gently several times until it becomes very sudsy. Be sure you do not squeeze the sponge dry. (The sponge should remain sudsy for insertion.)
4. Fold the sides of the sponge upward with a finger along each side to support it. The sponge should look long and narrow. Be sure the string loop dangles underneath the sponge from one end of the fold to the other, as shown.
5. Bend your wrist and point the end of the folded sponge toward your vagina. Be sure that you can see the fold when you look down at it and that the string loop dangles below.

6. From a standing position, squat down slightly and spread your legs apart. Use your free hand to spread apart the lips of the vagina. You may also stand with one foot on a stool or chair, sit cross-legged or lie down. The semi-squatting position seems to work best for most women. Slide the sponge into the opening of the vagina as far as your fingers will go. Let the sponge slide through your fingers, deeper into the vagina.

7. Now use one or two fingers to push the sponge gently up into your vagina as far as it will go. Be careful not to push a fingernail through the sponge. Check the position of the sponge by sliding your finger around the edge of the sponge to make sure your cervix is not exposed. You should be able to feel the string loop.

B. Questions about insertion of Today® Sponge.

1. How do I know Today® Sponge is in the proper position?

If you follow the instructions in this booklet, Today® Sponge should be positioned correctly in the upper vagina. To check its position, simply slide your finger around the edge of the sponge. If your cervix is not exposed, the sponge is in the proper position. You should be able to feel the string loop. If the sponge is out of position, simply slide it back in place.

2. Can Today® Sponge fall out?

It is unlikely that Today® Sponge will fall out. During a bowel movement or other form of internal straining, it may be pushed down to the opening of the vagina and perhaps fall out. If you suspect this happening, simply insert your finger into your vagina and push it back. If it should fall into the toilet, moisten a new sponge and insert it immediately. Do not flush the old sponge down the toilet. Discard it in a waste container.

3. How does Today® Sponge stay in place?

Today® Sponge is held in place by the muscles of the upper vagina. In addition, the cup-like indentation on the top of the sponge helps to keep it in position directly over the cervix.

10. How to remove Today Vaginal Contraceptive Sponge

A. Removal Procedure

1. Always wait 6 hours after your last act of intercourse before removing the sponge.

2. Put your finger into your vagina and reach up and back to find the string loop. If you cannot find the loop immediately, bear down until you feel the loop (see "Bearing Down," section 8D). Hook your finger around the loop. (If you have not found the loop, grasp the sponge between your thumb and forefinger.)

3. Slowly and gently pull the sponge out. If the vaginal muscles seem to be holding it tightly, wait a few minutes and try again. If removal is still difficult, use the following exercise to relax your vaginal muscles: Tighten vaginal muscles as hard as you can and hold for 10 seconds, then relax and let go. Repeat. As you relax, breathe out slowly while bearing down (see section 8D). Now remove the sponge as you continue to relax.

4. Dispose of the sponge in a waste container. Do not flush it down the toilet.

B. Special Removal Situations

1. Stuck Sponge

There are no structures in the vagina to interfere with removal of the sponge. With tension or unusually strong muscular pressure, the sponge may be held in the vagina more tightly than normal. Simple relaxation of the vaginal muscles and bearing down should make it possible to remove the sponge without difficulty (see section 8D).

If you are still unable to remove the sponge, it may have adhered by suction to the cervix. To remove, it is necessary to break the suction. To do this, slip a finger between the sponge and the cervix on one side, tilting the sponge up and away from the cervix. Once free, the sponge may be removed normally.

If none of the above suggestions seems to help, see your physician or family planning clinic. You may wish to take several unused Today® Sponges along so your medical advisor can help you refine your insertion and removal technique.

2. Upside-down Sponge

Occasionally, a sponge will turn upside down in the vagina, making the string loop more difficult to find. To find the string loop, run your finger around the edge on the back side of the sponge until you feel the string loop where it's attached to the sponge.

If you cannot find the string loop, simply grasp the edge of the sponge between your thumb and forefinger and pull it out slowly. Bearing down (section 8D) will make it easier to reach the sponge.

3. Torn Sponge

Today® Sponge, like a soft contact lens, should be handled gently. Pulling too hard or too quickly on the removal loop may cause the sponge to tear.

The procedure for removing a torn sponge is similar to that for an upside-down sponge. The important thing is to remove the sponge slowly. If you suspect that you have left small pieces of sponge inside the vagina, run a finger around the upper vault of your vagina with a sweeping movement and then toward the vaginal opening to find and remove any remaining sponge material. To reduce the risk of infection, it is important that you get all parts of sponge out of the vagina. If you have difficulty getting parts of sponge out of the vagina, call the Mayer Labs Product Support Line at 1-877-494-2525 or contact a health professional right away.

C. Questions about removal of Today® Sponge.

1. Is it necessary to douche after removing Today® Sponge?

No, it is not necessary. However, you may douche after using the sponge if you like. But do not douche while the sponge is inside the vagina. And always wait at least 6 hours after intercourse before removing the sponge.

2. Can Today® Sponge get lost in my body?

The opening from the vagina to the uterus is far too small for Today® Sponge to pass through. There is no other normal opening in the vagina that would provide access to any other part of your body.

TODAY®
sponge

C
VAGINAL
CONTRACEPTIVE
sponge

Manufactured for:
Mayer Laboratories, Inc.
1950 Addison Street, Berkeley, CA 94704, USA

www.TodaySponge.com / 1-877-494-2525

Today is a registered trademark
of Almatica Pharma, Inc.

Made in U.S.A
© 2011 Mayer Laboratories, Inc

PRINCIPAL DISPLAY PANEL - 3 Sponge Pouch Box

NO "PILL" SIDE EFFECTS
Hormone Free
24-Hour Protection

NDC 44376-100-01

TODAY®
sponge

C
VAGINAL
CONTRACEPTIVE
sponge

Intended for the prevention of pregnancy

3 vaginal contraceptive sponges
containing nonoxynol 9

3-WAY
PROTECTION!